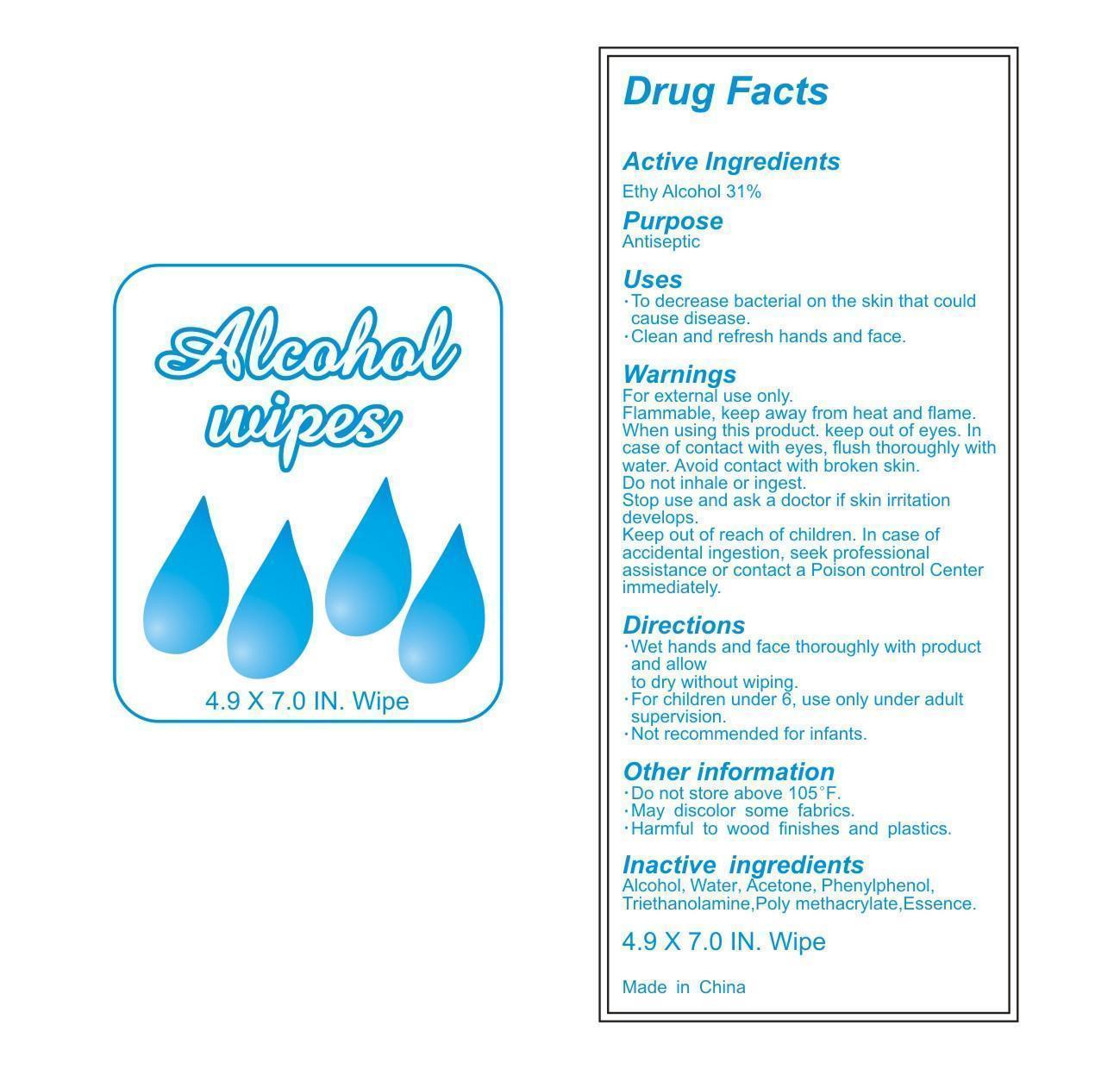 DRUG LABEL: Alcohol Wipes
NDC: 71734-202 | Form: CLOTH
Manufacturer: JIANGMEN SHUIZIRUN SANITARY ARTICLES CO., LTD.
Category: otc | Type: HUMAN OTC DRUG LABEL
Date: 20171009

ACTIVE INGREDIENTS: Alcohol .31 mL/1 mL
INACTIVE INGREDIENTS: Aloe Vera Leaf; Propylene Glycol; Water; TROLAMINE

DRUG FACTS

Active Ingredient

Ethyl Alcohol 31% (v/v)

Purpose

Antiseptic

Uses:

- To decrease bacterial on the skin that could cause disease.
- Clean and refresh hands and face.

WARNINGS

For external use only.

DO NOT USE

- Flammable, keep away from heat and flame.
- When using this product, keep out of eyes. In case of eye contact, flush thoroughly with water.
- Avoid contact with broken skin.
- Do not inhale or ingest.
- Stop use and ask a doctor if skin irritation develops.

Keep out of reach of children.

In case of accidental ingestion, seek professional assistance or contact a Poison Control Center immediately.

Directions:

- Wet hands and face thoroughly with product and allow to dry without wiping
- For children under 6, use only under adult supervision.
- Not recommended for infants.

Other Information:

- do not store above 105 F.
- may discolor some fabrics
- harmful to wood finishes and plastics

Inactive Ingredients:

alcohol, water, acetone, phenylphenol, triethanolamine, poly methacrylate, essence

Principal Display Panel – Case Label

Alcohol WIPES